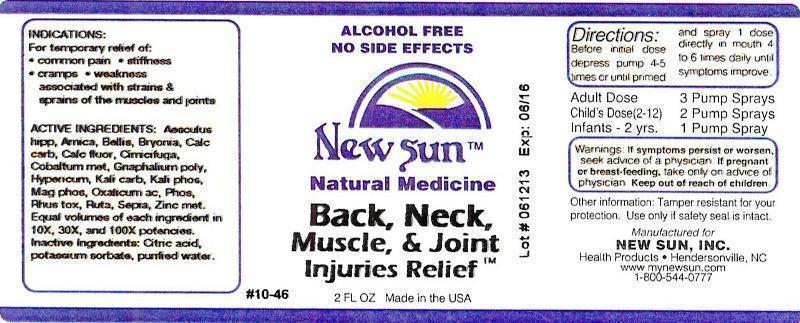 DRUG LABEL: Back, Neck, Muscle, and Joint Injuries Relief
NDC: 66579-0028 | Form: LIQUID
Manufacturer: New Sun Inc.
Category: homeopathic | Type: HUMAN OTC DRUG LABEL
Date: 20140908

ACTIVE INGREDIENTS: HORSE CHESTNUT 10 [hp_X]/59 mL; ARNICA MONTANA 10 [hp_X]/59 mL; BELLIS PERENNIS 10 [hp_X]/59 mL; BRYONIA ALBA ROOT 10 [hp_X]/59 mL; OYSTER SHELL CALCIUM CARBONATE, CRUDE 10 [hp_X]/59 mL; CALCIUM FLUORIDE 10 [hp_X]/59 mL; BLACK COHOSH 10 [hp_X]/59 mL; COBALT 10 [hp_X]/59 mL; PSEUDOGNAPHALIUM OBTUSIFOLIUM 10 [hp_X]/59 mL; HYPERICUM PERFORATUM 10 [hp_X]/59 mL; POTASSIUM CARBONATE 10 [hp_X]/59 mL; POTASSIUM PHOSPHATE, DIBASIC 10 [hp_X]/59 mL; MAGNESIUM PHOSPHATE, DIBASIC TRIHYDRATE 10 [hp_X]/59 mL; OXALIC ACID DIHYDRATE 10 [hp_X]/59 mL; PHOSPHORUS 10 [hp_X]/59 mL; TOXICODENDRON PUBESCENS LEAF 10 [hp_X]/59 mL; RUTA GRAVEOLENS FLOWERING TOP 10 [hp_X]/59 mL; SEPIA OFFICINALIS JUICE 10 [hp_X]/59 mL; ZINC 10 [hp_X]/59 mL
INACTIVE INGREDIENTS: CITRIC ACID MONOHYDRATE; POTASSIUM SORBATE; WATER

Back, Neck, Muscle, and Joint Injuries Relief

DOSAGE AND ADMINISTRATION

Directions: Before initial dose depress pump 4-5 times or until primed and spray 1 dose directly in mouth 4 to 6 times daily until symptoms improve.

Adult Dose: 3 Pump Sprays

Child's Dose (2-12): 2 Pump Sprays

Infants - 2 yrs: 1 Pump Spray

WARNINGS

Warnings: If symptoms persist or worsen, seek advice of a physician. If pregnant or breast-feeding, take only on advice of physician.

Keep out of reach of children.

Other information: Tamper resistant for your protection. Use only if safety seal is intact.

PURPOSE

Indications: For temporary relief of: •common pain •stiffness •cramps •weakness associated with strains and sprains of the muscles and joints

ACTIVE INGREDIENT

Active Ingredients: Aesculus hippocastanum, Arnica montana, Bellis perennis, Bryonia, Calcarea carbonica, Calcarea fluorica, Cimicifuga racemosa, Cobaltum metallicum, Gnaphalium polycephalum, Hypericum perforatum, Kali carbonicum, Kali phosphoricum, Magnesia phosphorica, Oxalicum acidum, Phosphorus, Rhus toxicodendron, Ruta graveolens, Sepia, Zincum metallicum. Equal volumes of each ingredient in 10X, 30X, 100X potencies.

Inactive Ingredient: Citric acid, potassium sorbate, purified water.

Indications: For temporary relief of:

- common pain
- stiffness
- cramps
- weakness associated with strains and sprains of the muscles and joints